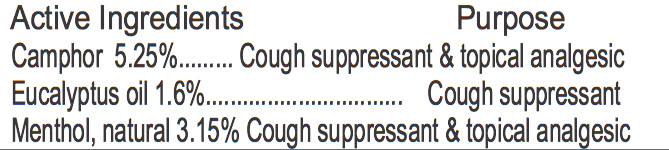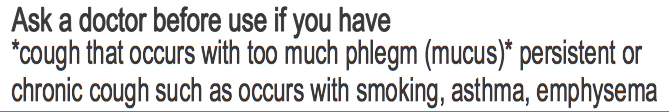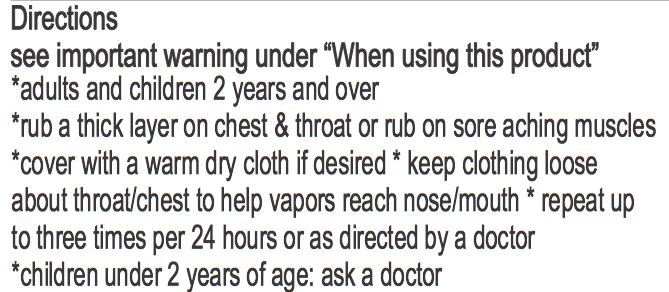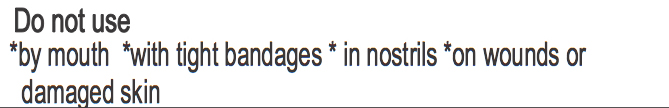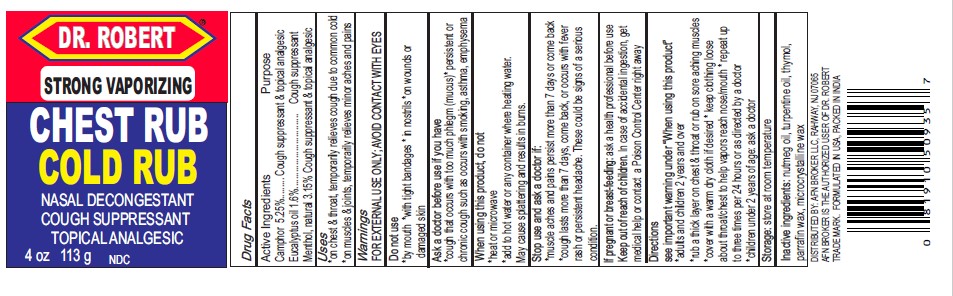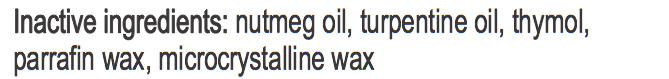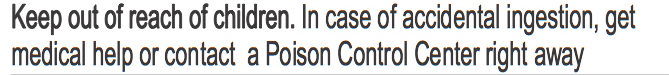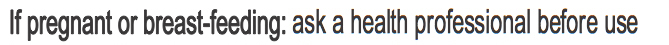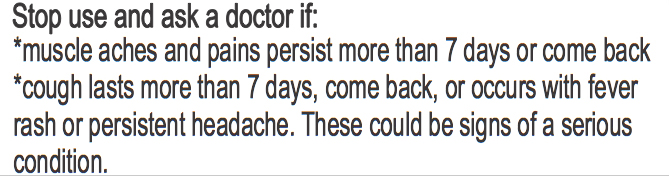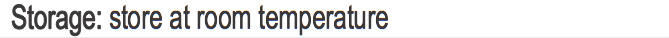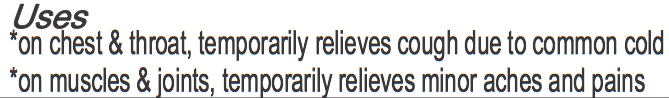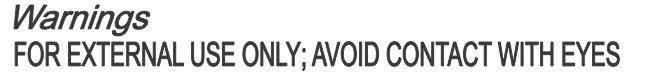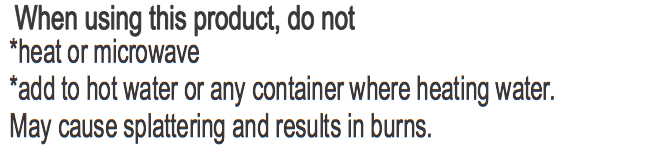 DRUG LABEL: STRONG VAPORIZING
NDC: 72004-001 | Form: OINTMENT
Manufacturer: AFN BROKER LLC.
Category: otc | Type: HUMAN OTC DRUG LABEL
Date: 20190110

ACTIVE INGREDIENTS: EUCALYPTUS OIL 1.6 g/100 g; MENTHOL 3.15 g/100 g; CAMPHOR (SYNTHETIC) 5.25 g/100 g
INACTIVE INGREDIENTS: NUTMEG OIL 0.006 g/100 g; TURPENTINE OIL; THYMOL 0.001 g/100 g; PARAFFIN 0.14 g/100 g; MICROCRYSTALLINE CELLULOSE 0.05 g/100 g

DRUG FACTS

ACTIVE INGREDIENTS

CAMPHOR 5.25%..............................COUGH SUPPRESSANT & TOPICAL ANALGESIC

EUCALYPTUS OIL 1.6%................................COUGH SUPPRESSANT

MENTHOL, NATURAL 3.15%..............................COUGH SUPPRESSANT & TOPICAL ANALGESIC

DO NOT USE

*BY MOUTH

*WITH TIGHT BANDAGES

*IN NOSTRILS

*ON WOUNDS OR DAMAGED SKIN

ASK A DOCTOR BEFORE USE IF YOU HAVE

*COUGH THAT OCCURS WITH TOO MUCH PHLEGM (MUCUS)* PERSISTENT OR CHRONIC COUGH SUCH AS OCCURS WITH SMOKING, ASTHMA, EMPHYSEMA

KEEP OUT OF REACH OF CHILDREN

IN CASE OF ACCIDENTAL INGESTION, GET MEDICAL HELP OR CONTACT A POISON CONTROL CENTER RIGHT AWAY

WARNINGS

FOR EXTERNAL USE ONLY; AVOID CONTACT WITH EYES

IF PREGNANT OR BREAST-FEEDING

ASK A HEALTH PROFESSIONAL BEFORE USE

USE

*ON CHEST & THROAT, TEMPORARILY RELIEVES COUGH DUE TO COMMON COLD

*ON MUSCLES & JOINTS, TEMPORARILY RELIEVES MINOR ACHES AND PAIN

WHEN USING THIS PRODUCT, DO NOT

*HEAT OR MICROWAVE

*ADD TO HOT WATER OR ANY CONTAINER WHERE HEATING WATER

MAY CAUSE SPLATTERING AND RESULTS IN BURNS

STOP USE AND ASK A DOCTOR IF

*MUSCLE ACHES AND PAINS PERSIST MORE THAN 7 DAYS OR COME BACK

*COUGH LASTS MORE THAN 7 DAYS, COME BACK, OR OCCURS IWTH FEVER RASH OR PERSISTENT HEADACHE.

THESE COULD BE SIGNS OF A SERIOUS CONDITION

STORAGE

STORE AT ROOM TEMPERATURE

DIRECTIONS

SEE IMPORTANT WARMING UNDER "WHEN USING THIS PRODUCT"

*ADULTS AND CHILDREN 2 YEARS AND OVER

*RUB A THICK LAYER ON CHEST & THROAT OR RUB ON SORE ACHING MUSCLES

*COVER WITH A WARM DRY CLOTH IF DESIRED

*KEEP CLOTHING LOOSE ABOUT THROAT/CHEST TO HELP VAPORS REACH NOSE/MOUTH

*REPEAT UP TO THREE TIMES PER 24 HOUSES OR AS DIRECTED BY A DOCTOR

*CHILDREN UNDER 2 YEARS OF AGE: ASK A DOCTOR

INACTIVE INGREDIENTS

NUTMEG OIL, TURPENTINE OIL, THYMOL, PARRAFIN WAX, MICROCRYSTALLINE WAX

PURPOSE

COUGH SUPPRESSANT & TOPICAL ANALGESIC